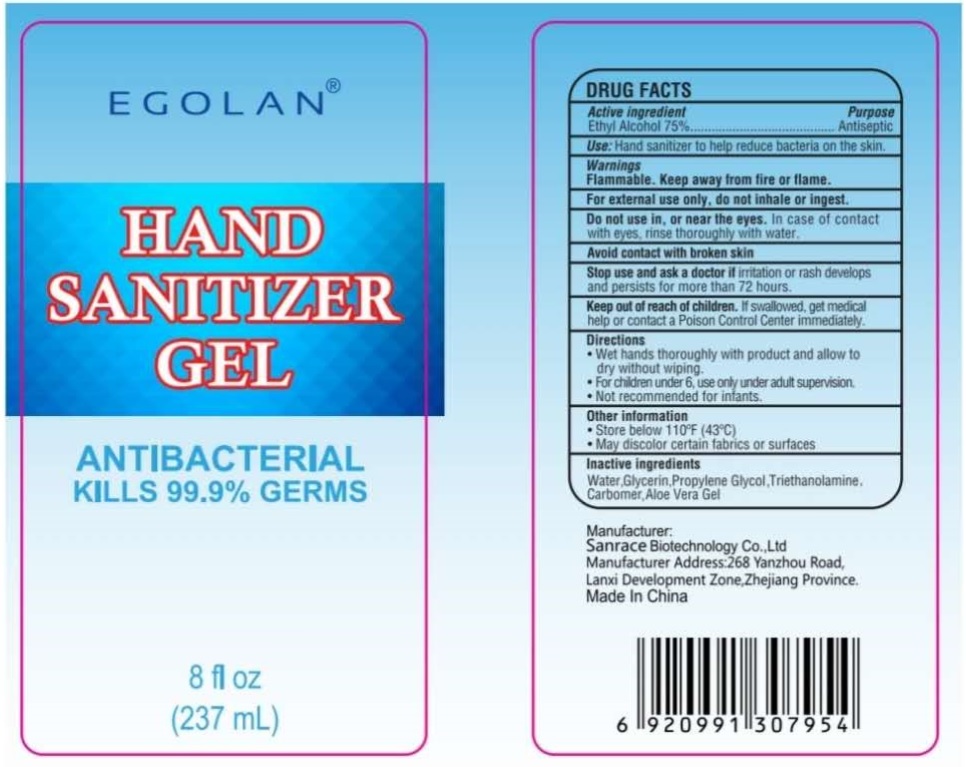 DRUG LABEL: EGOLAN
NDC: 75448-023 | Form: GEL
Manufacturer: Sanrace Biotechnology Co., Ltd.
Category: otc | Type: HUMAN OTC DRUG LABEL
Date: 20200615

ACTIVE INGREDIENTS: ALCOHOL 75 mL/100 mL
INACTIVE INGREDIENTS: WATER; GLYCERIN; PROPYLENE GLYCOL; TROLAMINE; CARBOMER HOMOPOLYMER, UNSPECIFIED TYPE; ALOE VERA LEAF

EGOLAN® HAND SANITIZER GEL

Active ingredient

Ethyl Alcohol 75%

Purpose

Antiseptic

INDICATIONS AND USAGE

Use: Hand sanitizer to help reduce bacteria on the skin.

Warnings

Flammable. Keep away from fire or flame.

For external use only. do not inhale or ingest.

Do not use in, or near the eyes. In case of contact with eyes, rinse thoroughly with water.

Avoid contact with broken skin

Stop use and ask a doctor if irritation or rash develops and persists for more than 72 hours.

Keep out of reach of children. If swallowed, get medical help or contact a Poison Control Center immediately.

Directions

• Wet hands thoroughly with product and allow to dry without wiping.

• For children under 6, use only under adult supervision

• Not recommended for infants

Other Information

• Store below 110°F (43°C)

• May discolor certain fabrics or surfaces

Inactive ingredients

Water,Glycerin,Propylene Glycol,Triethanolamine,Carbomer,Aloe Vera Gel

ANTIBACTERIAL

KILLS 99.9% GERMS

Manufacturer:

Sanrace Biotechnology Co., Ltd

Manufacturer Address:268 Yanzhou Road,

Lanxi Development Zone,Zhejiang Province.

Made In China.